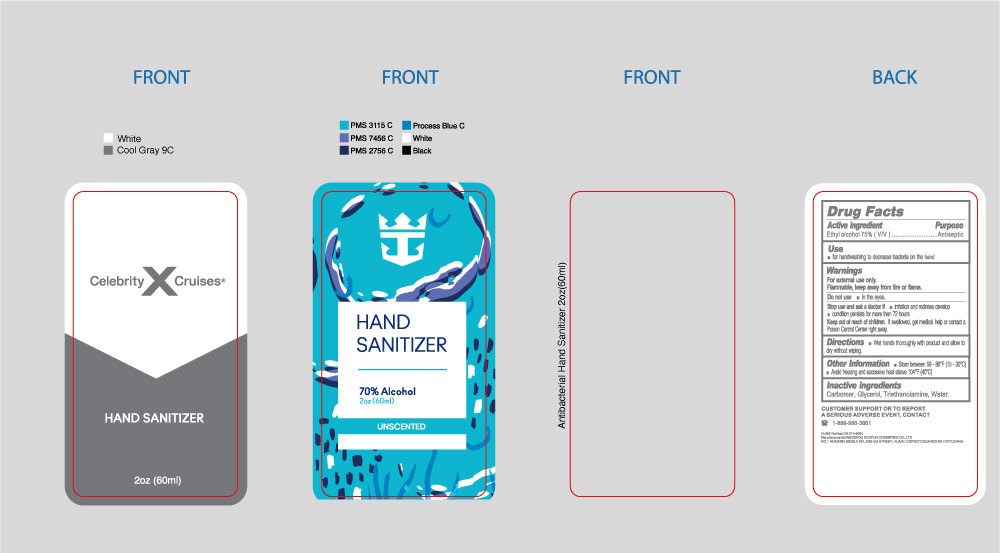 DRUG LABEL: Antibacterial Hand Sanitizer
NDC: 77027-777 | Form: GEL
Manufacturer: Guangzhou Zuofun Cosmetics Co., Ltd
Category: otc | Type: HUMAN OTC DRUG LABEL
Date: 20201006

ACTIVE INGREDIENTS: ALCOHOL 0.75 mL/1 mL
INACTIVE INGREDIENTS: CARBOMER HOMOPOLYMER, UNSPECIFIED TYPE; GLYCERIN; TROLAMINE; WATER

Antibacterial Hand Sanitizer

Active ingredient

Ethyl alcohol 75%

Purpose

Antiseptic

Use

- for handwashing to decrease bacteria on the hand

Warnings

For external use only.
Flammable，keep away from fire or flame.

Do not use

- in the eyes.

Stop use and ask a doctor if

- irritation and redness develop
- condition persists for more than 72 hours

Keep out of reach of children.

If swallowed, get medical help or contact a Poison Control Center right away.

Directions

- Wet hands thoroughly with product and allow to dry without wiping.

Other information

- Store between 59 - 86°F(15 - 30°C)
- Avoid freezing and excessive heat above 104°(40°C)

Inactive ingredients

Carbomer, Glycerol, Triethanolamine, Water.